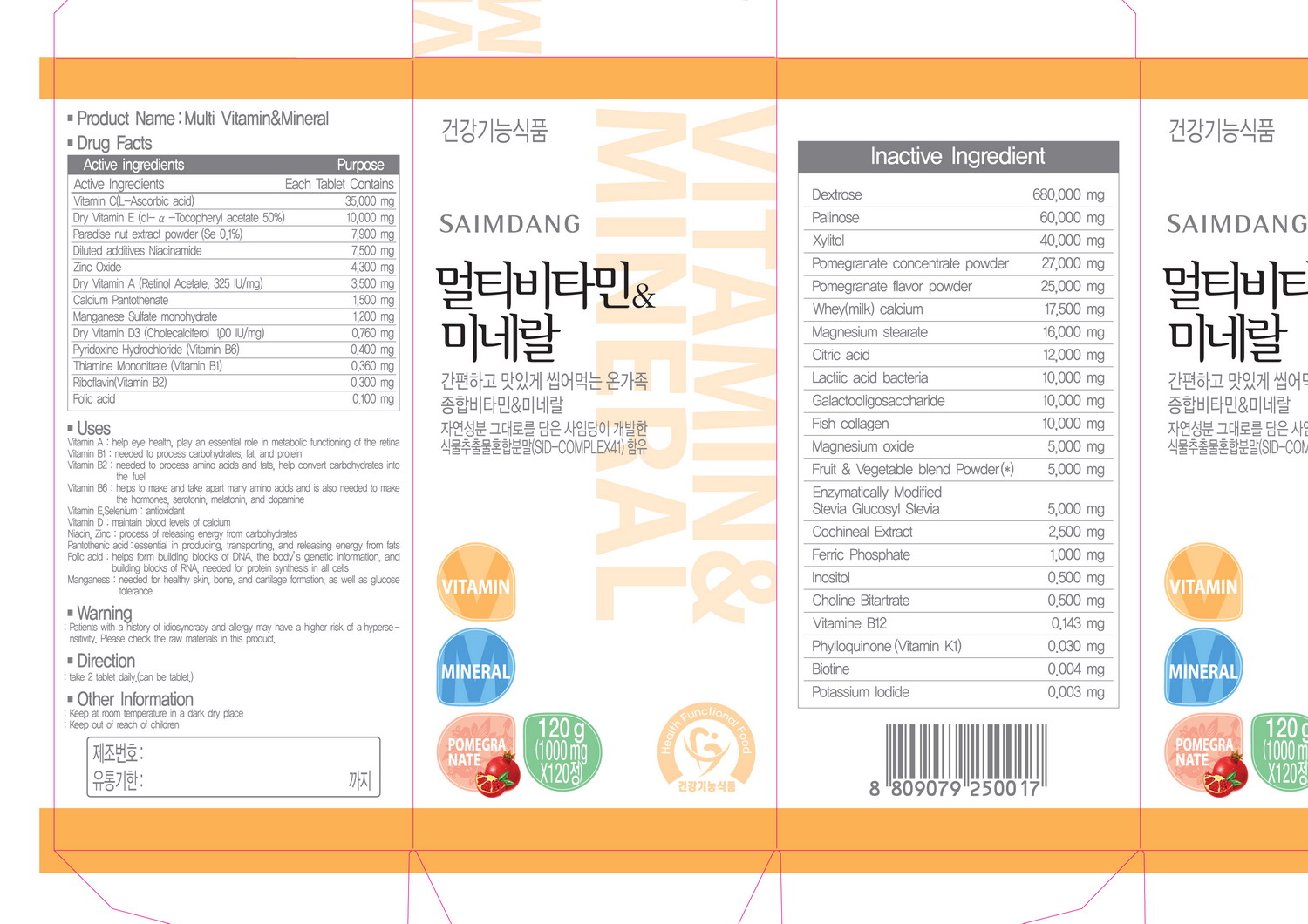 DRUG LABEL: Multi Vitamin and Mineral
NDC: 51220-2001 | Form: TABLET, CHEWABLE
Manufacturer: Saimdang Cosmetics Co., Ltd
Category: otc | Type: HUMAN OTC DRUG LABEL
Date: 20100821

ACTIVE INGREDIENTS: ASCORBIC ACID 35 mg/1 1; .ALPHA.-TOCOPHEROL ACETATE, D- 10 mg/1 1; NIACINAMIDE 7.5 mg/1 1; ZINC OXIDE 4.3 mg/1 1; VITAMIN A 3.5 mg/1 1; CALCIUM PANTOTHENATE 1.5 mg/1 1; MANGANESE 1.2 mg/1 1; MANGANESE 0.76 mg/1 1; PYRIDOXINE 0.4 mg/1 1; THIAMINE 0.36 mg/1 1; RIBOFLAVIN 0.3 mg/1 1; FOLIC ACID 0.1 mg/1 1

Drug Facts

ACTIVE INGREDIENT

Active ingredients: Vitamin C, Vitamin E, Niacinamide, Zinc Oxide, Vitamin A, Calcium, Manganese sulfate, Vitamin D3, Vitamin B6, Vitamin B1, Vitamin B2, Folic acid

• Uses
Vitamin A : helps eye health. play an essential role in metabolic functioning of the retina
Vitamin B1 : needed to process carbohydrates. fat, and protein
Vitarrin B2 : needed to process amino acids and fats, help convert carbohydrates into
the fuel
Vitamin B6 : heps to make and take apart many amino acids and is also needed to make
the hormones, serotonin, melatonin, and dopamine
Vitamin E,Selenium : antioxidant
Vitamin D: maintain blood levels of calcium
Niacin, Zinc : process of releasing energy from carbohydrates
Pantothenic acid :essential in producing, transporting, and releasing energy from fats
Folic acid : helps form building blocks of DNA, the body's genetic information, and
building blocks of RNA, needed for protein synthesis in all cells
Manganese : needed for healthy skin, bone, and cartilage formation, as well as glucose
tolerance
• Warning
: Patients with a history of idiosyncrasy and allergy may have a higher risk of a hypersensitivity,
Please check the raw materials in this product,
• Direction
: take 2 tablet daily (can be tablet)
• Other Information
: Keep at room temperature in a dark dry place
: Keep out of reach of children

• Uses
Vitamin A : helps eye health. play an essential role in metabolic functioning of the retina
Vitamin B1 : needed to process carbohydrates. fat, and protein
Vitarrin B2 : needed to process amino acids and fats, help convert carbohydrates into
the fuel
Vitamin B6 : heps to make and take apart many amino acids and is also needed to make
the hormones, serotonin, melatonin, and dopamine
Vitamin E,Selenium : antioxidant
Vitamin D: maintain blood levels of calcium
Niacin, Zinc : process of releasing energy from carbohydrates
Pantothenic acid :essential in producing, transporting, and releasing energy from fats
Folic acid : helps form building blocks of DNA, the body's genetic information, and
building blocks of RNA, needed for protein synthesis in all cells
Manganese : needed for healthy skin, bone, and cartilage formation, as well as glucose
tolerance

KEEP OUT OF REACH OF CHILDREN

• Caution
: Keep at room temperature in a dark dry place
: Keep out of reach of children

INDICATIONS AND USAGE

• Direction
: take 2 tablet daily (can be tablet)

• Warning
: Patients with a history of idiosyncrasy and allergy may have a higher risk of a hypersensitivity,
Please check the raw materials in this product,

DOSAGE AND ADMINISTRATION

• Direction
: take 2 tablet daily (can be tablet)

INACTIVE INGREDIENT

Inactive ingredients: dextrose, xylitol, pomegranate, calcium, magnesium, citric, lactic, oligosaccharide, stevia, cochineal, ferric phosphate, inositol, choline, vitamin B12, vitamin K1